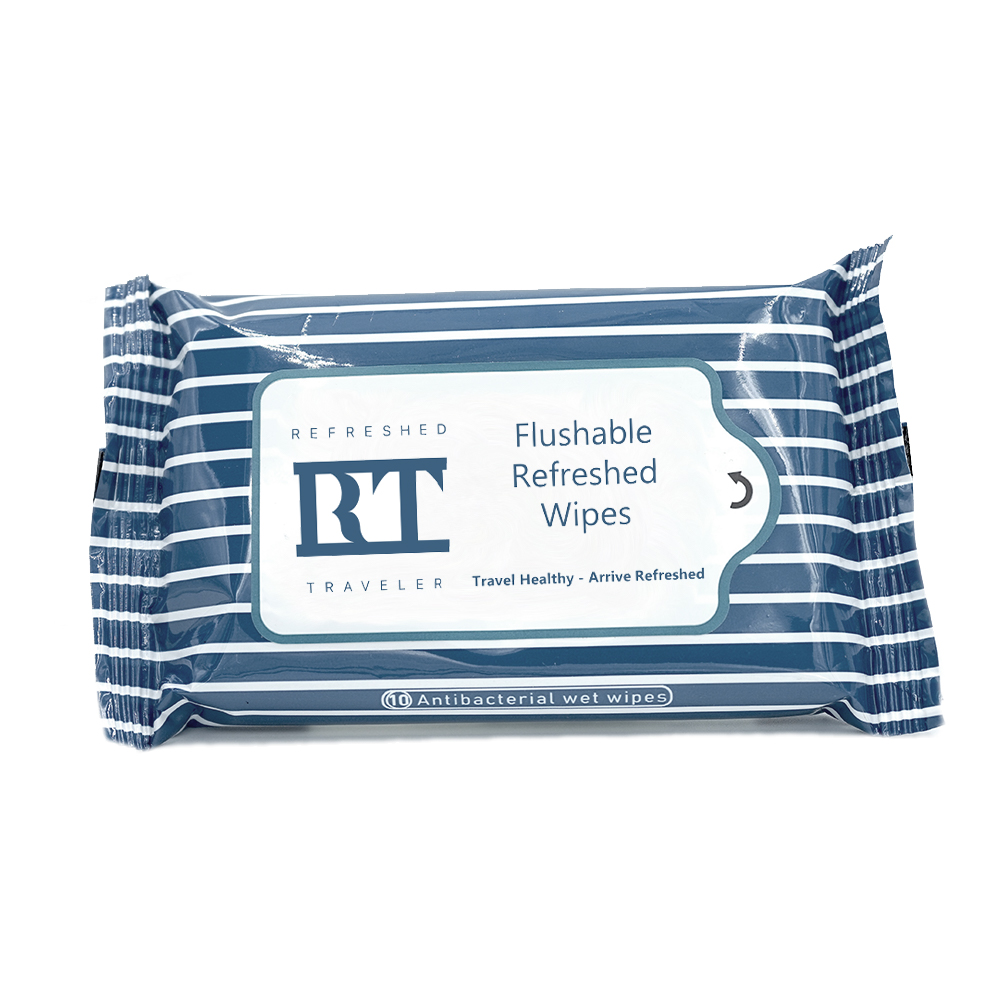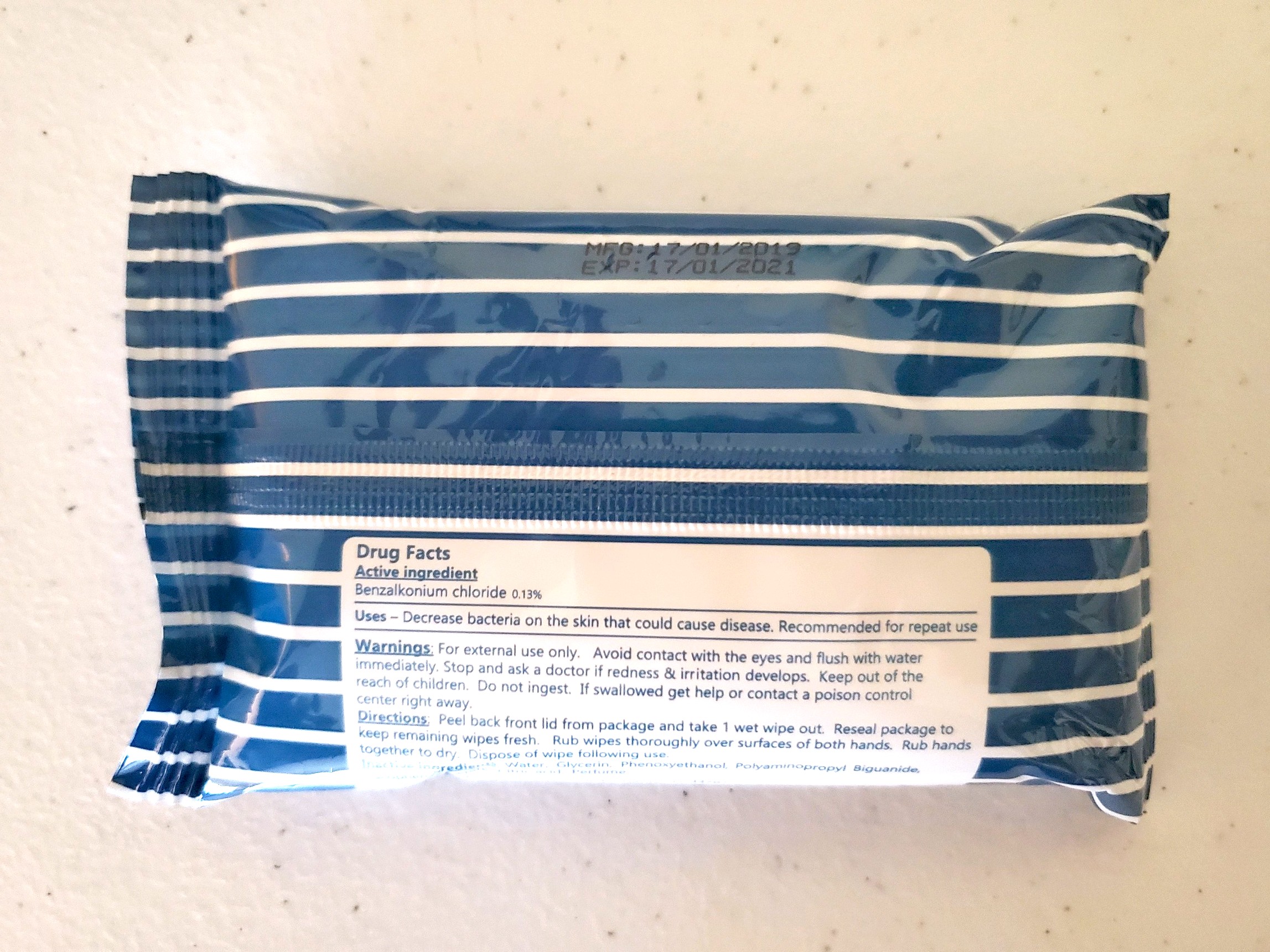 DRUG LABEL: Refresh Wipes
NDC: 72920-2018 | Form: CLOTH
Manufacturer: Plane It Safe LLC
Category: otc | Type: HUMAN OTC DRUG LABEL
Date: 20211224

ACTIVE INGREDIENTS: BENZALKONIUM CHLORIDE 0.13 g/100 g
INACTIVE INGREDIENTS: WATER

Refresh Wipes

ACTIVE INGREDIENT

Benzalkonium Chloride 0.13%

PURPOSE

Antiseptic

INDICATIONS AND USAGE

To decrease bacteria on the hands

WARNINGS

FOR EXTERNAL USE ONLY

-Keep away from eyes. In case of contact flush with water immediately. Stop and ask a doctor if redness and irritation develops. Keep out of the reach of children. Do not ingest. If swollowed get help or contact a poison control center right away.

DOSAGE AND ADMINISTRATION

Rub wipes throughly over surfaces of both hands. Rub hands together to dry.

INACTIVE INGREDIENT

Water, Glycerin, Phenoxyenthanol, Polyaminopropyl, Biguanide, Tocopherol Acetate, Citric acid, Parfum.

Stop use if irritation or redness develops

Keep out of the reach of children